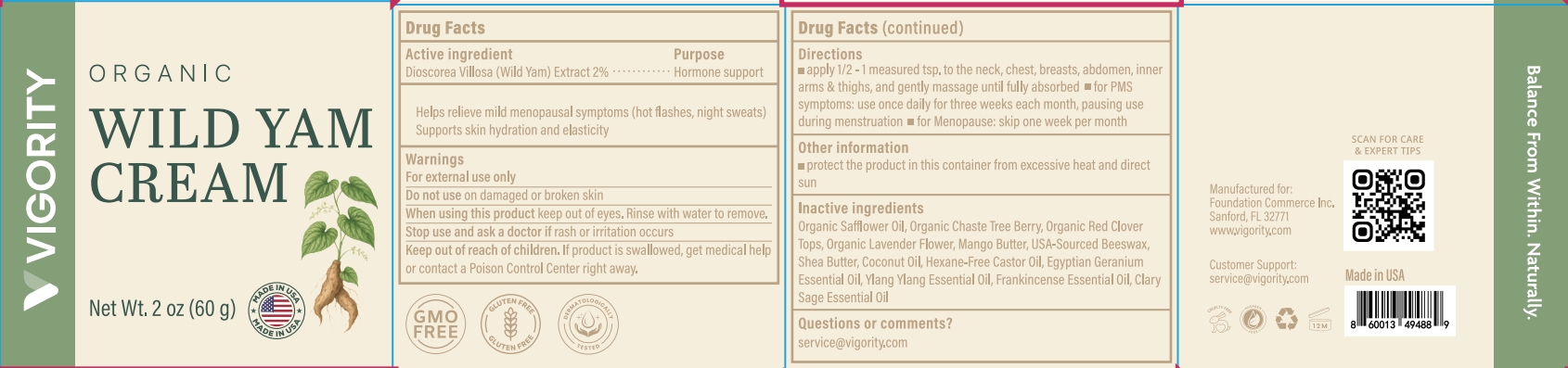 DRUG LABEL: Vigority Wild Yam Cream
NDC: 85739-002 | Form: CREAM
Manufacturer: FOUNDATION COMMERCE INC
Category: otc | Type: HUMAN OTC DRUG LABEL
Date: 20250730

ACTIVE INGREDIENTS: DIOSCOREA VILLOSA ROOT 1.2 g/60 g
INACTIVE INGREDIENTS: RED CLOVER; BEESWAX; MANGO SEED OIL; CLARY SAGE OIL; SHEA BUTTER; CHASTE TREE FRUIT; PELARGONIUM GRAVEOLENS FLOWER OIL; LAVANDULA ANGUSTIFOLIA (LAVENDER) FLOWER; COCONUT OIL; YLANG-YLANG OIL; FRANKINCENSE OIL; SAFFLOWER OIL; CASTOR OIL

Initial Drug Listing - Vigority Wild Yam Cream

ACTIVE INGREDIENT

Dioscorea Villosa (Wild Yam) Extract 2%

PURPOSE

Hormone support

INDICATIONS AND USAGE

Helps relieve mild menopausal symptoms (hot flashes, night sweats)Supports skin hydration and elasticity.

WARNINGS

For external use only

Do not use on damaged or broken skin

WHEN USING

keep out of eyes, Rinse with water to remove.

Stop use and ask a doctor if rash or irritation occurs

KEEP OUT OF REACH OF CHILDREN

lf product is swallowed, get medical helpor contact a Poison Control Center right away.

DOSAGE AND ADMINISTRATION

- apply 1/2 -1 measured tsp,to the neck, chest, breasts, abdomen, innerarms & thighs, and gently massage until fully absorbed.
- for PMSsymptoms: use once daily for three weeks each month, pausing useduring menstruation.
- for Menopause: skip one week per month.

OTHER SAFETY INFORMATION

protect the product in this container from excessive heat and direct sun

INACTIVE INGREDIENT

Organic Safflower Oil, Organic Chaste Tree Berry, Organic Red CloverTops, Organic Lavender Flower, Mango Butter, USA-Sourced Beeswax,Shea Butter, Coconut Oil, Hexane-Free Castor Oil, Egyptian Geranium Essential Oil, Ylang Ylang Essential 0il, Frankincense Essential Oil, Clary Sage Essential Oil

QUESTIONS

service@vigority.com